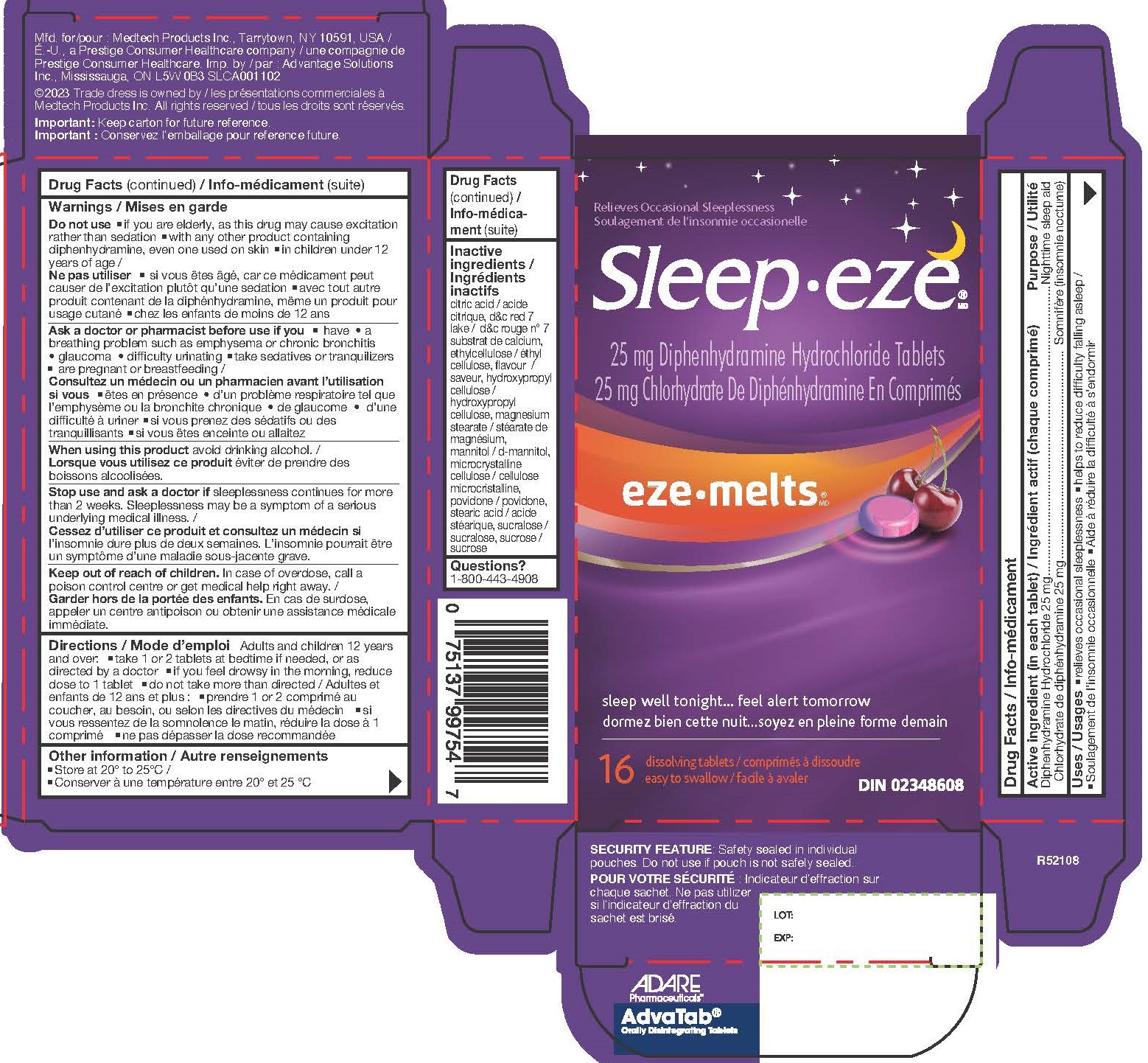 DRUG LABEL: Diphenhydramine Hydrochloride
NDC: 10267-4703 | Form: TABLET, ORALLY DISINTEGRATING
Manufacturer: Contract Pharmacal Corp.
Category: otc | Type: HUMAN OTC DRUG LABEL
Date: 20231201

ACTIVE INGREDIENTS: DIPHENHYDRAMINE HYDROCHLORIDE 25 mg/1 1
INACTIVE INGREDIENTS: SUCROSE; ANHYDROUS CITRIC ACID; MANNITOL; HYDROXYPROPYL CELLULOSE, UNSPECIFIED; SUCRALOSE; CHERRY; ETHYLCELLULOSES; MICROCRYSTALLINE CELLULOSE; CROSPOVIDONE; D&C RED NO. 7; MAGNESIUM STEARATE

4703- Export